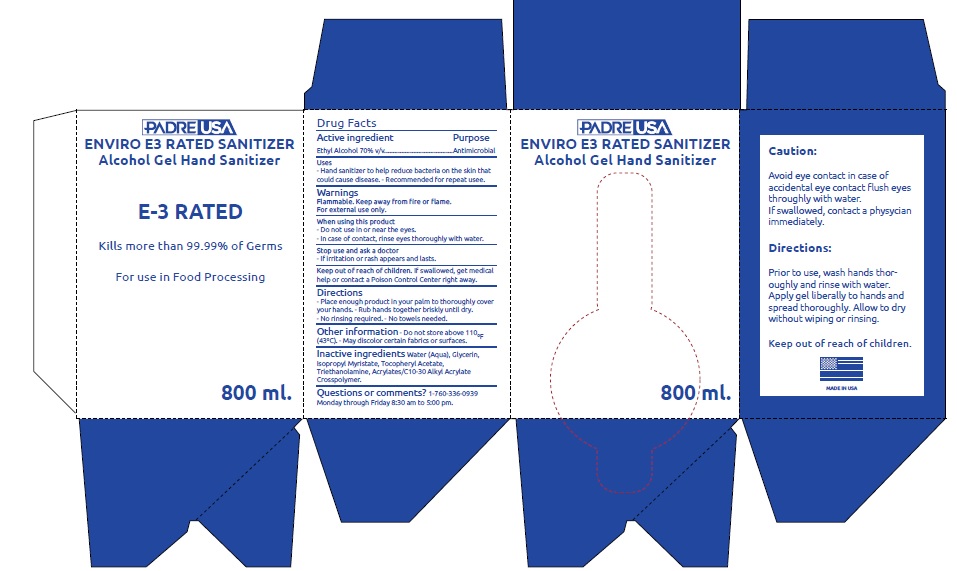 DRUG LABEL: ENVIRO E3 RATED SANITIZER
NDC: 74693-001 | Form: LIQUID
Manufacturer: IMPERIAL VALLEY DISTRIBUTING, INC
Category: otc | Type: HUMAN OTC DRUG LABEL
Date: 20200407

ACTIVE INGREDIENTS: ALCOHOL 70 mL/100 mL
INACTIVE INGREDIENTS: .ALPHA.-TOCOPHEROL ACETATE; WATER; GLYCERIN; CARBOMER HOMOPOLYMER, UNSPECIFIED TYPE; ISOPROPYL MYRISTATE; TROLAMINE; CARBOMER INTERPOLYMER TYPE A (ALLYL SUCROSE CROSSLINKED)

ENVIRO E3 RATED sanitizer

Active ingredient

Ethanol Alcohol 70% v/v

Purpose

Antimicrobial

Uses

- Hand sanitizer to help reduce bacteria on the skin that could cause disease.
- Recommended for repeat use.

Warnings

Flammable. Keep away from fire or flame

For external use only.

When using this product

- Do not use in or near the eyes.
- In case of contact, rinse eyes thoroughly with water.

Stop use and ask a doctor

- If irritation or rash appears and lasts.

Keep out of reach of children.

If swallowed, get medical help or contact a Poison Control Center right away.

Directions

- Place enough product in your palm to thoroughly cover your hands.
- Rub hands together briskly until dry.
- No rinsing required.
- No towels needed

Other information

Do not store above 110⁰F(43⁰C).

- May discolor certain fabrics or surfaces.

Inactive ingredients

Water, Glycerin, Isopropyl Myristate, Tocopheryl Acetate, Triethanolamine, Acrylates/C10-C30 Alkyl Akrylate, Crosspolymer